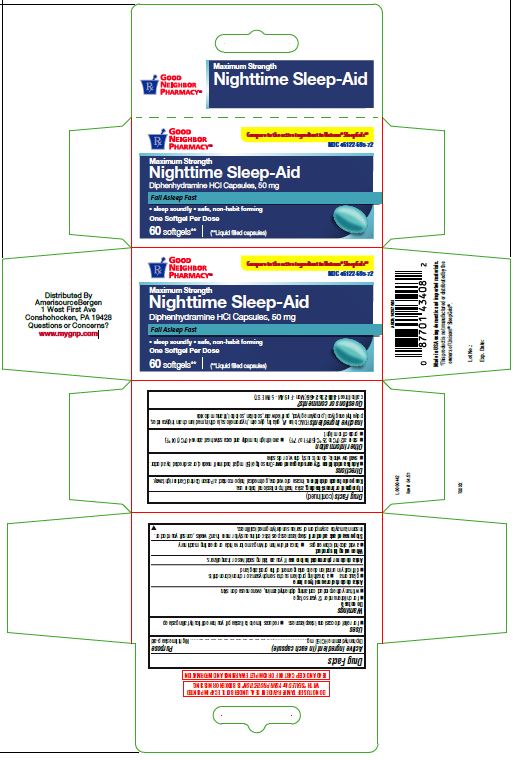 DRUG LABEL: Nighttime Sleep-Aid
NDC: 46122-695 | Form: CAPSULE, LIQUID FILLED
Manufacturer: AMERISOURCE BERGEN
Category: otc | Type: HUMAN OTC DRUG LABEL
Date: 20231010

ACTIVE INGREDIENTS: DIPHENHYDRAMINE HYDROCHLORIDE 50 mg/1 1
INACTIVE INGREDIENTS: GELATIN; GLYCERIN; LECITHIN, SOYBEAN; WATER; SORBITAN; MEDIUM-CHAIN TRIGLYCERIDES; TITANIUM DIOXIDE; POLYETHYLENE GLYCOL, UNSPECIFIED; FD&C BLUE NO. 1; HYPROMELLOSE, UNSPECIFIED

Drug Facts

Active ingredient (in each capsule)

Diphenhydramine HCl 50 mg

Purpose

Nighttime sleep-aid

Uses

■ for relief of occasional sleeplessness
■ reduces time to fall asleep if you have difficulty falling asleep

Warnings

Do not use

■ for children under 12 years of age
■ with any other product containing diphenhydramine, even one used on skin.

Ask a doctor before use if you have

■ glaucoma
■ a breathing problem such as emphysema or chronic bronchitis
■ difficulty in urination due to enlargement of the prostate gland

Ask a doctor or pharmacist before use

if you are taking sedatives or tranquilizers.

When using this product

■ avoid alcoholic beverages
■ be careful when driving a motor vehicle or operating machinery

Stop use and ask a doctor if

sleeplessness persists continuously for more than 2 weeks, consult your doctor. Insomnia may be a symptom of serious underlying medical illness.

If pregnant or breast-feeding,

ask a health professional before use.

Keep out of reach of children.

In case of overdose, get medical help or contact a Poison Control Centre right away.

Directions

■ Adults and children 12 years of age and over: One softgel (50 mg) at bedtime if needed, or as directed by a doctor.
■ swallow whole; do not crush, chew, or dissolve

Other information

■ store at 20°C to 25°C (68°F to 77°F)
■ avoid high humidity and excessive heat above 40°C (104°F).
■ protect from light

Inactive ingredients

FD&C blue #1, gelatin, glycerin, hypromellose, lecithin, medium chain triglycerides, polyethylene glycol, propylene glycol, purified water, sorbitan, sorbitol, titanium dioxide

Questions or comments?

call toll free 1-888-235-2466 (Mon - Fri 9AM - 5PM EST)

DO NOT USE IF TAMPER-EVIDENT SEAL UNDER BOTTLE CAP IMPRINTED

WITH “ SEALED for YOUR PROTECTION” IS BROKEN OR MISSING.

READ AND KEEP CARTON FOR COMPLETE WARNINGS AND INFORMATION

Made in USA using domestic and imported materials.

†This product is not manufactured or distributed by the

owners of Unisom® SleepGels®.

Lot No.:

Exp. Date:

Distributed By
AmerisourceBergen
1 West First Ave
Conshohocken, PA 19428
Questions or Concerns?
www.mygnp.com

L0000442

Rev # 04/21

60's Count Carton

GOOD

NEIGHBOR

PHARMACY®

Compare to the active ingredient in Unisom® SleepGels®†

NDC 46122-695-72

Maximum Strength

Nighttime Sleep-aid

Diphenhydramine HCl Capsules, 50 mg

Fall Asleep Fast
• sleep soundly • safe, non-habit forming

One Softgel Per Dose

60 softgels** I (**Liquid-filled capsules)